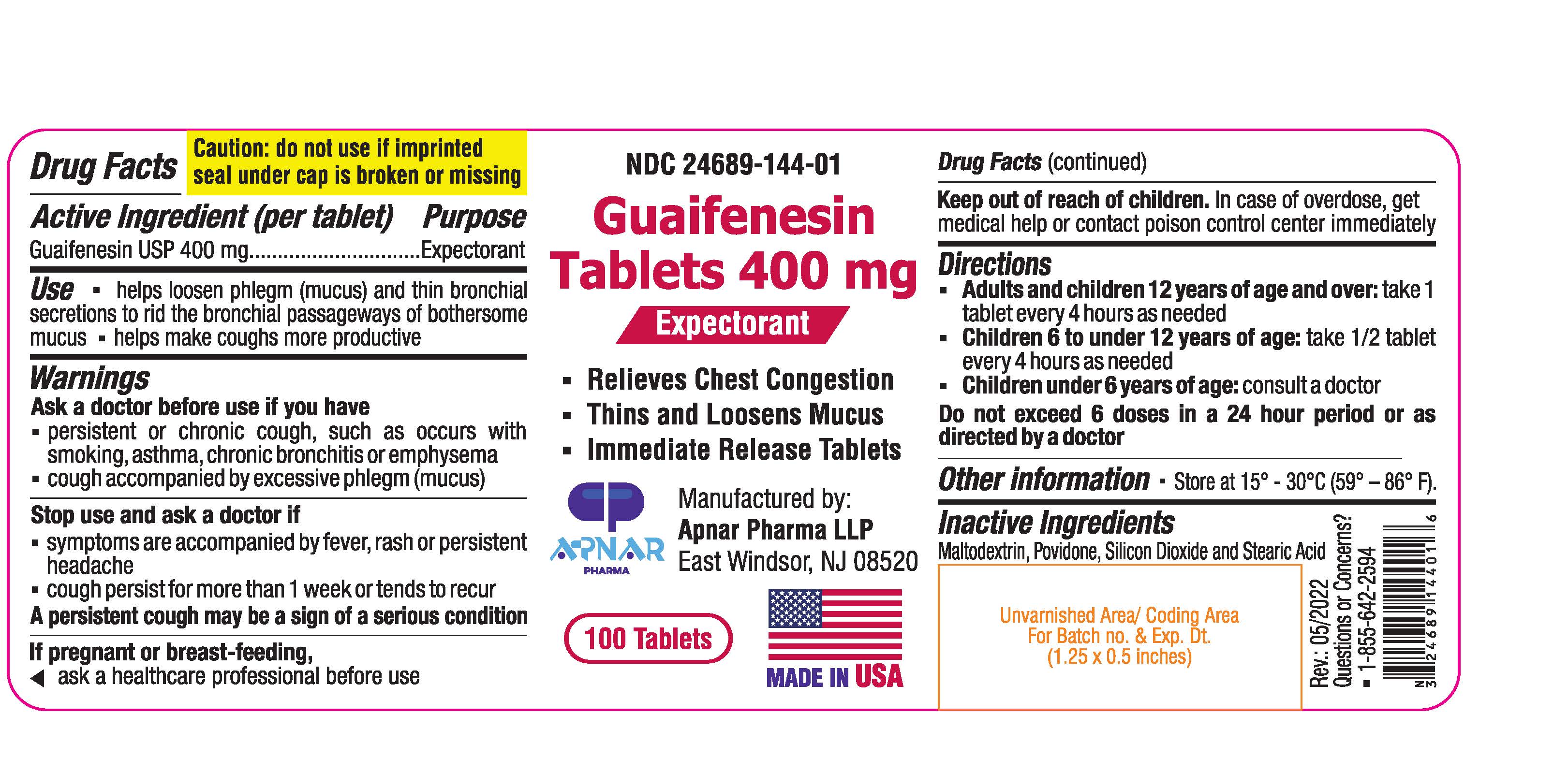 DRUG LABEL: Guaifenesin
NDC: 24689-144 | Form: TABLET
Manufacturer: APNAR PHARMA LP
Category: otc | Type: HUMAN OTC DRUG LABEL
Date: 20231021

ACTIVE INGREDIENTS: GUAIFENESIN 400 mg/1 1
INACTIVE INGREDIENTS: MALTODEXTRIN; SILICON DIOXIDE; STEARIC ACID; POVIDONE

Guaifenesin Tablets 400 mg

BOXED WARNING

Caution: do not use if imprinted seal under cap is broken or missing.

Active Ingredient (per tablet)

Guaifenesin USP 400 mg

Purpose

Expectorant

Use

- helps loosen phlegm (mucus) and thin bronchial secretions to rid the bronchial passageways of bothersome mucus
- helps make coughs more productive

Warnings

Ask doctor before use if you have

- persistent or chronic cough, such as occurs with smoking, asthma, chronic bronchitis or emphysema
- cough accompanied by excessive phlegm (mucus)

Stop use and ask a doctor if

- Symptoms are accompanied by fever, rash or persistent headache
- cough persists for more than 1 week or tends to recur

A persistent cough may be a sign of a serious condition

If pregnant or breast-feeding, ask a healthcare professional before use.

Keep out of reach of children.

In case of overdose, get medical help or contact Poison Control Center immediately.

Directions

- Adults and children 12 years of age and over: take 1 tablet every 4 hours as needed
- Children 6 to under 12 years of age: take 1/2 tablet every 4 hours as needed
- Children under 6 years of age: consult a doctor

Do not exceed 6 doses in a 24 hour period or as directed by a doctor

Other Information

Store at 15°-30°C (59°-86°F)

Inactive Ingredients

Maltodextrin, Povidone, Silicon dioxide and Stearic acid

Questions or concerns?

- 1-855-642-2594

Manufactured by:

APNAR PHARMA LLP

East Windsor, NJ 08520

Made in USA

Rev.: 05/2022

PACKAGE LABEL

NDC 24689-144-01

Guaifenesin Tablets 400 mg

Expectorant

100 Tablets